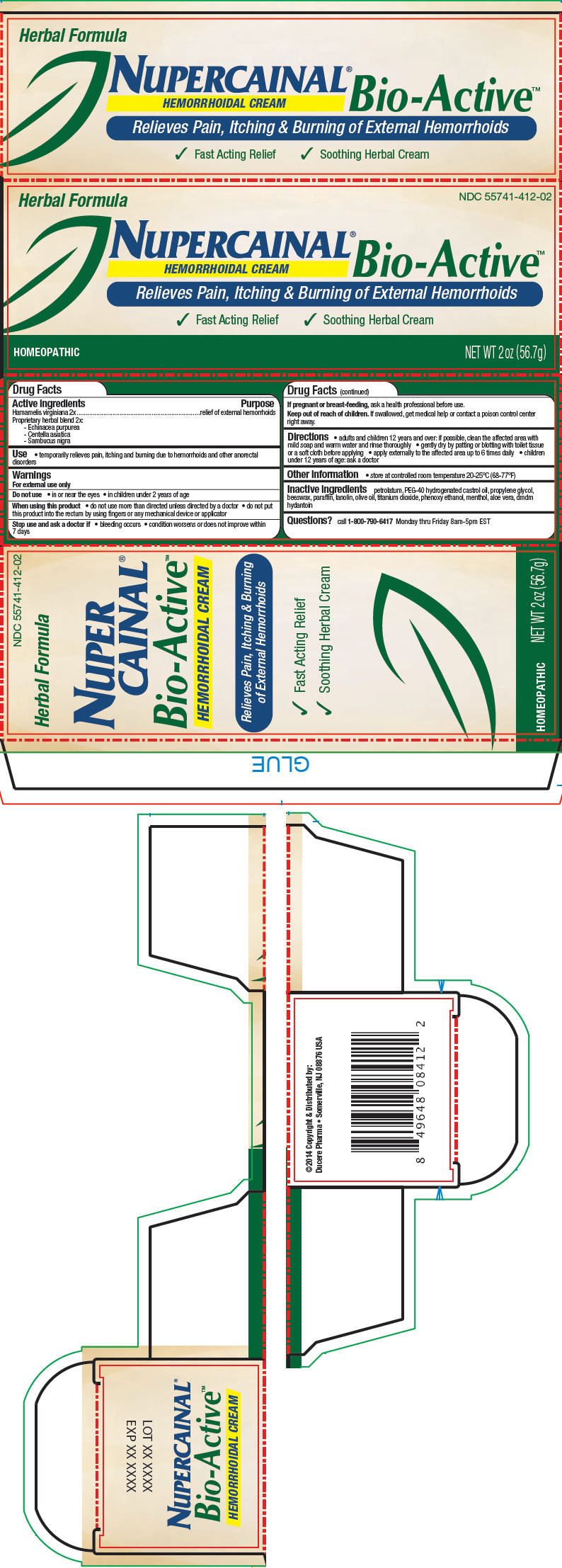 DRUG LABEL: Nupercainal Bio-Active Hemorrhoidal
NDC: 55741-412 | Form: CREAM
Manufacturer: Ducere Pharma
Category: homeopathic | Type: HUMAN OTC DRUG LABEL
Date: 20140418

ACTIVE INGREDIENTS: Hamamelis Virginiana Root Bark/Stem Bark 5 g/100 g; Echinacea purpurea 5 g/100 g; Centella asiatica 5 g/100 g; Sambucus Nigra Flowering Top 5 g/100 g
INACTIVE INGREDIENTS: petrolatum; Polyoxyl 40 Hydrogenated Castor Oil; propylene glycol; yellow wax; paraffin; lanolin; olive oil; titanium dioxide; phenoxyethanol; menthol; aloe vera leaf; dmdm hydantoin

Nupercainal® Bio-Active™ Hemorrhoidal Cream

Drug Facts

Active ingredients

Hamamelis virginiana 2x
Proprietary herbal blend 2x:

1. Echinacea purpurea
2. Centella asiatica
3. Sambucus nigra

Purpose

relief of external hemorrhoids

Use

- temporarily relieves pain, itching and burning due to hemorrhoids and other anorectal disorders

Warnings

For external use only

Do not use

- in or near the eyes
- in children under 2 years of age

When using this product

- do not use more than directed unless directed by a doctor
- do not put this product into the rectum by using fingers or any mechanical device or applicator

Stop use and ask a doctor if

- bleeding occurs
- condition worsens or does not improve within 7 days

PREGNANCY OR BREAST FEEDING

If pregnant or breast-feeding, ask a health professional before use.

Keep out of reach of children. If swallowed, get medical help or contact a poison control center right away.

Directions

- adults and children 12 years and over: if possible, clean the affected area with mild soap and warm water and rinse thoroughly
- gently dry by patting or blotting with toilet tissue or a soft cloth before applying
- apply externally to the affected area up to 6 times daily
- children under 12 years of age: ask a doctor

Other information

- store at controlled room temperature 20-25°C (68-77°F)

Inactive ingredients

petrolatum, PEG-40 hydrogenated castrol oil, propylene glycol, beeswax, paraffin, lanolin, olive oil, titanium dioxide, phenoxy ethanol, menthol, aloe vera, dmdm hydantoin

Questions?

call 1-800-790-6417 Monday thru Friday 8am-5pm EST

Distributed by:
Ducere Pharma • Somerville, NJ 08876 USA

PRINCIPAL DISPLAY PANEL - 56.7 g Tube Carton

Herbal Formula

NDC 55741-412-02

NUPERCAINAL®
Bio-Active™
HEMORRHOIDAL CREAM

Relieves Pain, Itching & Burning of External Hemorrhoids

✓ Fast Acting Relief ✓ Soothing Herbal Cream

HOMEOPATHIC

NET WT 2 oz (56.7g)